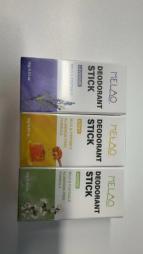 DRUG LABEL: Deodorant Stick
NDC: 83566-565 | Form: STICK
Manufacturer: Guangzhou Yilong Cosmetics Co., Ltd
Category: otc | Type: HUMAN OTC DRUG LABEL
Date: 20240807

ACTIVE INGREDIENTS: 1,2-PROPYLENE UREA 9 g/100 g; GLYCERIN 1,2-DIMETHYL ETHER 6 g/100 g
INACTIVE INGREDIENTS: WATER O-15 59 g/100 g; SODIUM STEARATE 5 g/100 g; POLYSORBATE 20 5 g/100 g; POLYSORBATE 60 4 g/100 g

Active ingredients

Propylene Glycol 9%

Glycerin 6%

Purpose

Deodorization

INACTIVE ingredients

Water59%

Sodium Stearate5%

Polysorbate 20 5%

Polysorbate 60 4%

Tetrasodium EDTA3.70%

Parfum3.60%

Phenoxyethanol2.40%

Lavandula Angustifolia(lavender)Extract2.30%

Warnings

For extemnal use only

Stop use and ask a doctor if

rash occurs

Uses

STEP1: Clean and thoroughly dry your skin.

STEP2: Twist the bottom of the product.

STEP3: Gently apply to the underarms or other desired areas

Keep out of reach of children

lf swallowed, get medical help or contact a Poison Control Center right away.

Do not use

on damaged or broken skin

When using this product

keep out of eyes. Rinse with water to remove

DOSAGE

Twist out an appropriate amount of Deodorant Stick and spread evenly on skin